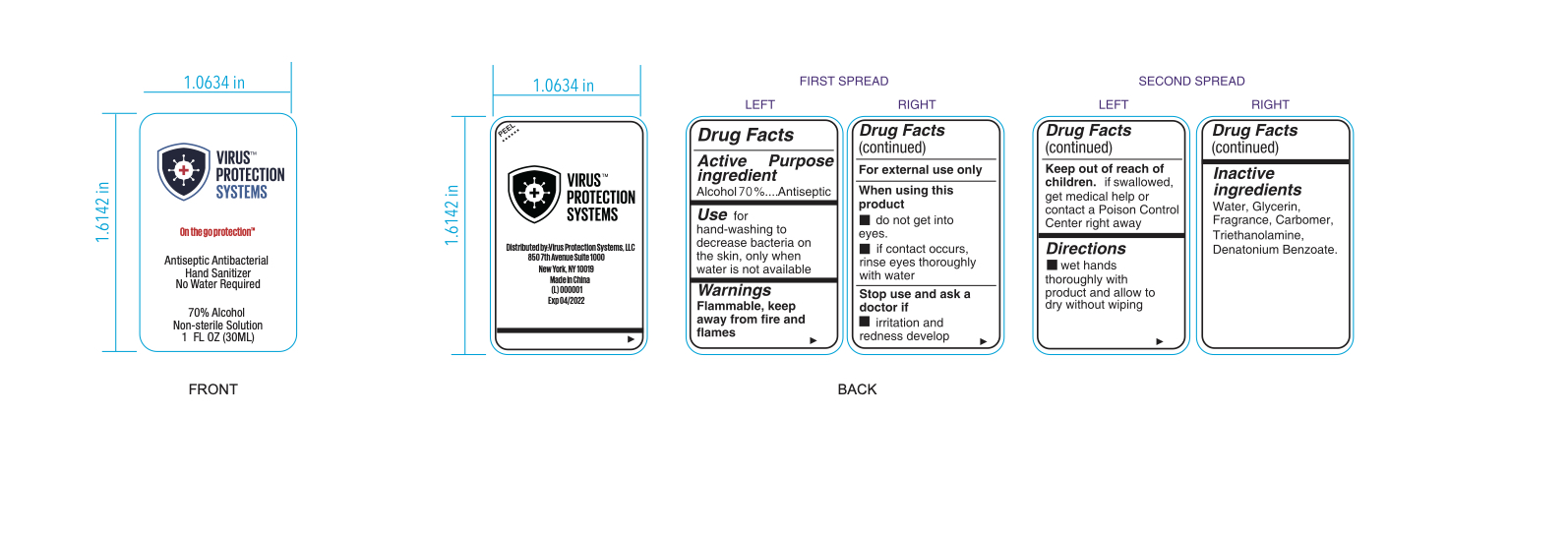 DRUG LABEL: Hand Sanitizer
NDC: 74707-001 | Form: LIQUID
Manufacturer: Virus Protection Systems LLC
Category: otc | Type: HUMAN OTC DRUG LABEL
Date: 20200518

ACTIVE INGREDIENTS: ALCOHOL 70 mL/100 mL
INACTIVE INGREDIENTS: CARBOMER 1342 0.4 mL/100 mL; 2-((DIMETHYLAMINO)METHYL)-1,3-DIPHENYL-1-PROPANOL, ERYTHRO- 0.4 mL/100 mL; WATER 29.2 mL/100 mL

Hand Sanitizer 30ML

Active Ingredient(s)

Alcohol 70% - Antiseptic

Purpose

Antiseptic, Hand Sanitizer

Use

for hand-washing to decrease bacteria on the skin, only when water is not available

Warnings

For external use only. Flammable. Keep away from heat or flame

When using this product keep do not get into the eyes, ears, and mouth. If contact occurs rinse eyes thoroughly with water.
Stop use and ask a doctor if irritation or redness develop
Keep out of reach of children. If swallowed, get medical help or contact a Poison Control Center right away.

Stop use and ask a doctor if irritation and redness develop

Keep out of reach of children. If swallowed, get medical help or contact a Poison Control Center right away.

Directions

wet hands thoroughly with product and allow to dry without wiping

Other information

Not Tested on Animals

Inactive ingredients

Glycerin Fragrance, Carbomer, Triethanolamine, Denatonium Benzoate

Package Label - Principal Display Panel

On the go protection

Antiseptic Antibacterial

Hand Sanitizer

No Water Required

70% Alcohol

Non Sterile Solution

30 mL